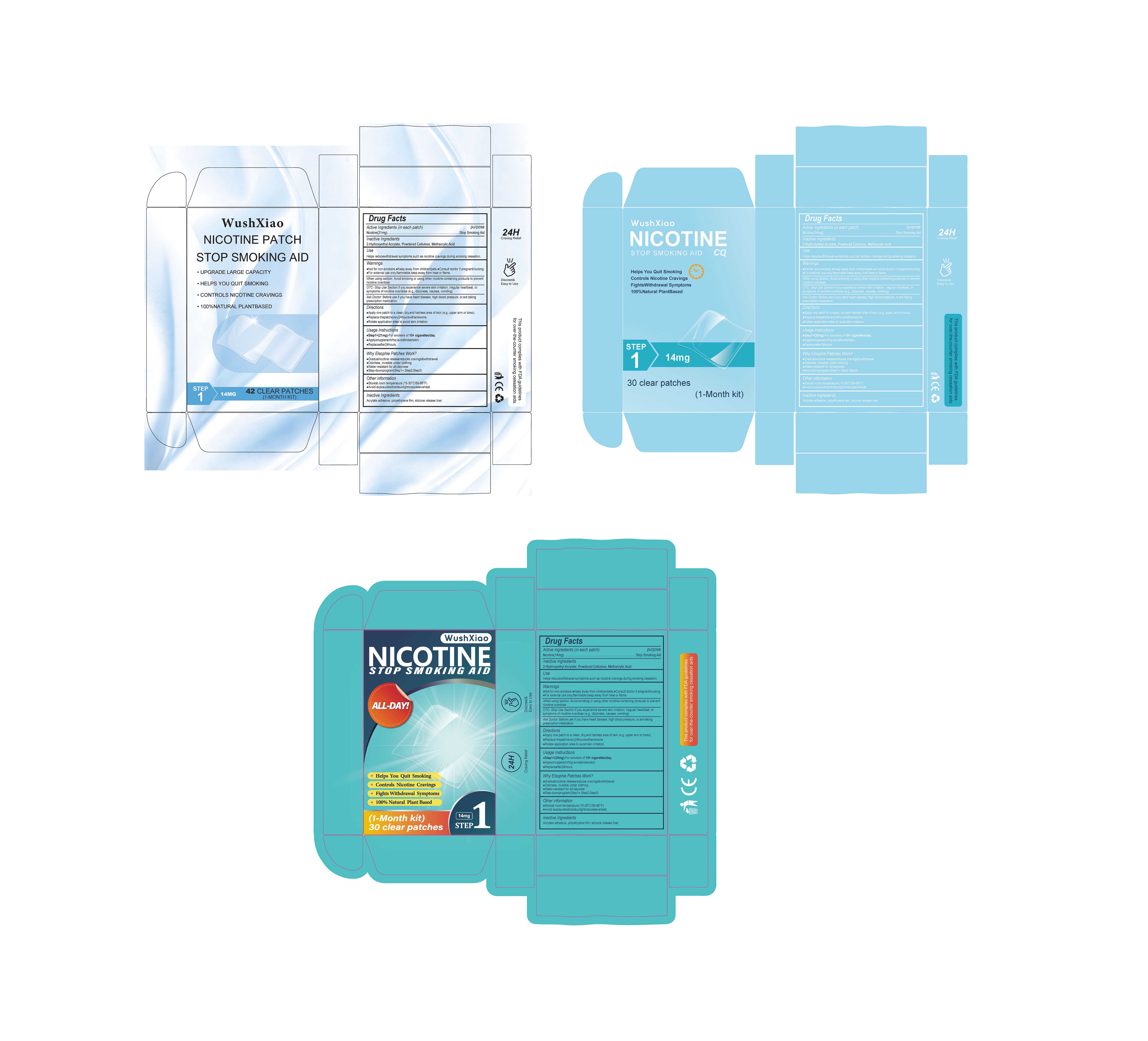 DRUG LABEL: NICOTINE STOP SMOKING AID
NDC: 84735-013 | Form: PATCH
Manufacturer: Hengyang Chuangjiujia Trading Co., Ltd.
Category: otc | Type: HUMAN OTC DRUG LABEL
Date: 20251105

ACTIVE INGREDIENTS: NICOTINE 14 mg/1 1
INACTIVE INGREDIENTS: METHACRYLIC ACID; 2-HYDROXYETHYL ACRYLATE; POWDERED CELLULOSE

84735-013 NICOTINE STOP SMOKING AID

ACTIVE INGREDIENT

Ncotine(14mg)

PURPOSE

Stop Smoking Aid

INDICATIONS AND USAGE

Helps reducewithdrawal symptoms ,such as nicotine cravings,during smoking cessation.

WARNINGS

Not for non-smokers. Keep away from chlldrenfpets. Consult doctor if pregnant/nursing
For external use only,flammable,keep awav from heat or flame.

WHEN USING

When using sectlon, Avoid smoking or using other nicotine-containing products to prevent nicotine overdose.

Ask Docfor, Before use if you have heart disease, high blood pressure, or.are taking prescription medication

STOP USE

OTC- Stop Use Section lf you experience severe skin irritation, rregular heartbeat, or. svmptoms of nicotine overdose (e.g. dizziness nausea vomiting)

DOSAGE AND ADMINISTRATION

Apply one patch to a cean, dry,and hairless area of skin (e.g.upper arm or torso).
Replace thepatchever24hourswithanewone
Rotate application sites to avoid skin irritation

INACTIVE INGREDIENT

2-Hydroxyethyl Acrlate,Powdered Cellulose, Methacrylic Acid

KEEP OUT OF REACH OF CHILDREN SECTION